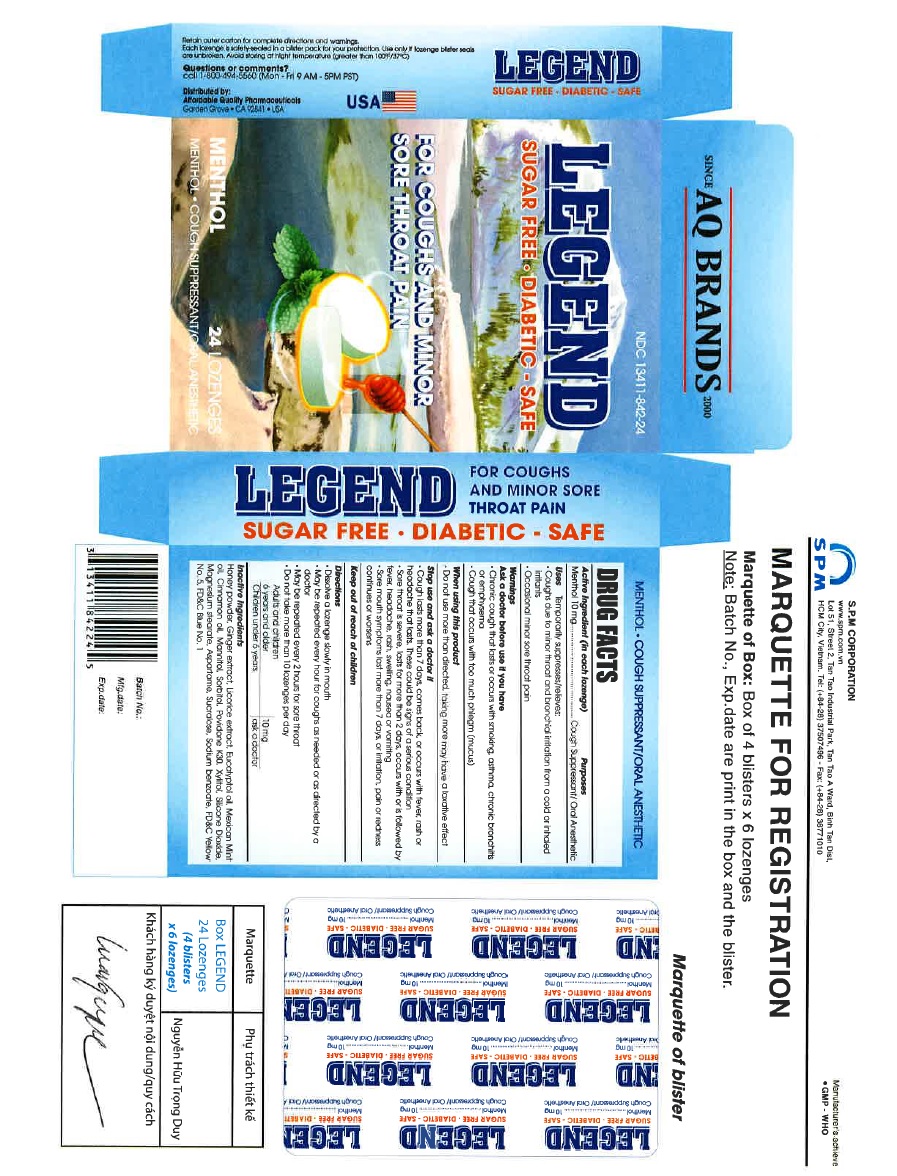 DRUG LABEL: LEGEND COUGH lozenge
NDC: 13411-842 | Form: LOZENGE
Manufacturer: Advanced Pharmaceutical Services, Inc. Dba Affordable Quality Pharmaceuticals
Category: otc | Type: HUMAN OTC DRUG LABEL
Date: 20200415

ACTIVE INGREDIENTS: MENTHOL 10 mg/1 1
INACTIVE INGREDIENTS: HONEY; GINGER; LICORICE; EUCALYPTOL; PLECTRANTHUS AMBOINICUS WHOLE; CINNAMON OIL; MANNITOL; Sorbitol; Povidone K30; Xylitol; SILICON DIOXIDE; Magnesium stearate; Aspartame; Sucralose; Sodium benzoate; FD&C Yellow No. 5; FD&C Blue No. 1

LEGEND

Active Ingredient

Menthol

Purpose

Cough Suppressant/ Oral Anesthetic

Uses

Temporarily suppresses/relieves:

- Coughs due to minor throat and bronchial irritation from a cold or inhaled irritant
- Occasional minor sore throat pain

Warnings

Ask a doctor before use if you have

- Chronic cough that lasts or occurs with smoking, asthma, chronic bronchitis or emphysema
- Cough that occurs with too much phlegm (mucus)

When using this product

Do not use more than directed, taking more may have a laxative effect

Stop use and ask a doctor if

- Cough lasts more than 7 days, comes back, or occurs with fever, rash or headache that lasts.These could be signs of a serious condition
- Sore throat is severe, lasts for more than 2 days, occurs with or is followed by fever, headache, rash, swelling, nausea or vomiting
- Sore mouth symptoms last more than 7 days, or irritation, pain or redness continues or worsens

Directions

- Dissolve a lozenge slowly in mouth.
- May be repeated every hour for coughs as needed or as directed by a doctor.
- May be repeated every 2 hours for sore throat.
- Do not take more than 10 lozenges per day.

Keep out of reach of children

- Adults and children 6 years and older 10 mg
- Children under 6 years ask a doctor

Inactive Ingredients

Honey powder, Ginger extract, Licorice extract, Eucalyptol oil, Mexican Mint oil, Cinnamon oil, Mannitol, Sorbitol, Povidone K30, Xylitol, Silicone Dioxide, Magnesium stearate, Aspartame, Sucralose, Sodium benzoate, FD&C Yellow No. 5, FD&C Blue No. 1